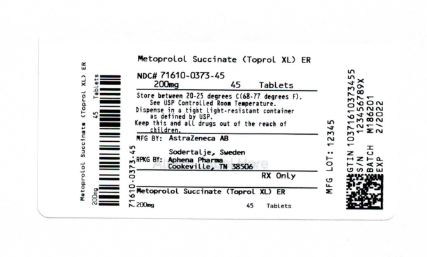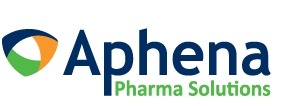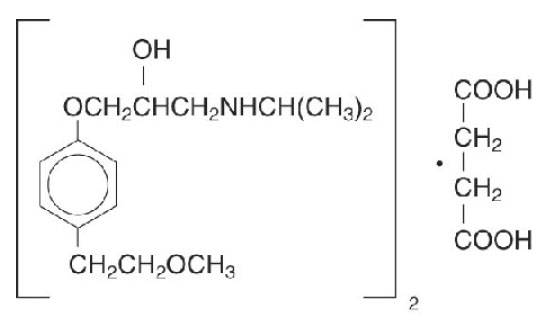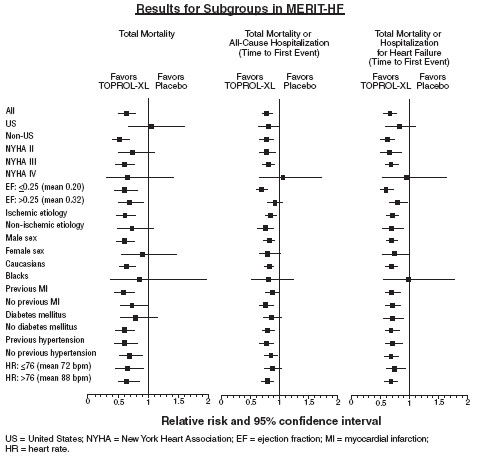 DRUG LABEL: TOPROL
NDC: 71610-373 | Form: TABLET, EXTENDED RELEASE
Manufacturer: Aphena Pharma Solutions - Tennessee, LLC
Category: prescription | Type: HUMAN PRESCRIPTION DRUG LABEL
Date: 20200113

ACTIVE INGREDIENTS: METOPROLOL SUCCINATE 200 mg/1 1
INACTIVE INGREDIENTS: SILICON DIOXIDE; SODIUM STEARYL FUMARATE; POLYETHYLENE GLYCOL 6000; TITANIUM DIOXIDE; PARAFFIN; HYPROMELLOSES

HIGHLIGHTS OF PRESCRIBING INFORMATION

These highlights do not include all the information needed to use TOPROL-XL® safely and effectively. See full prescribing information for TOPROL-XL.
TOPROL-XL® (metoprolol succinate) Tablet, Extended-Release for Oral Use
Initial U.S. Approval: 1992

WARNING: ISCHEMIC HEART DISEASE

See full prescribing information for complete boxed warning.

Following abrupt cessation of therapy with beta-blocking agents, exacerbations of angina pectoris and myocardial infarction have occurred. Warn patients against interruption or discontinuation of therapy without the physician’s advice. (5.1)

1 INDICATIONS AND USAGE

TOPROL-XL, metoprolol succinate, is a beta1-selective adrenoceptor blocking agent.

TOPROL-XL is indicated for the treatment of:

- Hypertension, to lower blood pressure. Lowering blood pressure reduces the risk of fatal and non-fatal cardiovascular events, primarily strokes and myocardial infarctions. (1.1)
- Angina Pectoris. (1.2)
- Heart Failure - for the treatment of stable, symptomatic (NYHA Class II or III) heart failure of ischemic, hypertensive, or cardiomyopathic origin. (1.3)

2 DOSAGE AND ADMINISTRATION

- Administer once daily. Dosing of TOPROL-XL should be individualized. (2)
- Heart Failure: Recommended starting dose is 12.5 mg or 25 mg doubled every two weeks to the highest dose tolerated or up to 200 mg. (2.3)
- Hypertension: Usual initial dosage is 25 to 100 mg once daily. The dosage may be increased at weekly (or longer) intervals until optimum blood pressure reduction is achieved. Dosages above 400 mg per day have not been studied. (2.1)
- Angina Pectoris: Usual initial dosage is 100 mg once daily. Gradually increase the dosage at weekly intervals until optimum clinical response has been obtained or there is an unacceptable bradycardia. Dosages above 400 mg per day have not been studied. (2.2)
- Switching from immediate-release metoprolol to TOPROL-XL: use the same total daily dose of TOPROL-XL. (2)

3 DOSAGE FORMS AND STRENGTHS

- TOPROL-XL Extended-Release Tablets (metoprolol succinate): 25 mg, 50 mg, 100 mg and 200 mg. (3)

4 CONTRAINDICATIONS

- Known hypersensitivity to product components. (4)
- Severe bradycardia. (4)
- Heart block greater than first degree. (4)
- Cardiogenic shock. (4)
- Decompensated cardiac failure. (4)
- Sick sinus syndrome without a pacemaker. (4)

5 WARNINGS AND PRECAUTIONS

- Heart Failure: Worsening cardiac failure may occur. (5.2)
- Bronchospastic Disease: Avoid beta blockers. (5.3)
- Pheochromocytoma: If required, first initiate therapy with an alpha blocker. (5.4)
- Major Surgery: Avoid initiation of high-dose extended-release metoprolol in patients undergoing non-cardiac surgery because it has been associated with bradycardia, hypotension, stroke and death. Do not routinely withdraw chronic beta blocker therapy prior to surgery. (5.5, 6.1)
- Diabetes and Hypoglycemia: May mask tachycardia occurring with hypoglycemia. (5.6)
- Patients with Hepatic Impairment: (5.7)
- Thyrotoxicosis: Abrupt withdrawal in patients with thyrotoxicosis might precipitate a thyroid storm. (5.8)
- Anaphylactic Reactions: Patients may be unresponsive to the usual doses of epinephrine used to treat allergic reaction. (5.9)
- Peripheral Vascular Disease: Can aggravate symptoms of arterial insufficiency. (5.10)
- Calcium Channel Blockers: Because of significant inotropic and chronotropic effects in patients treated with beta-blockers and calcium channel blockers of the verapamil and diltiazem type, caution should be exercised in patients treated with these agents concomitantly. (5.11)

6 ADVERSE REACTIONS

- Most common adverse reactions: tiredness, dizziness, depression, shortness of breath, bradycardia, hypotension, diarrhea, pruritus, rash. (6.1)

To report SUSPECTED ADVERSE REACTIONS, contact Aralez Pharmaceuticals US Inc. at 1-833-694-8235 or FDA at 1-800-FDA-1088 or www.fda.gov/medwatch.

7 DRUG INTERACTIONS

- Catecholamine-depleting drugs may have an additive effect when given with beta-blocking agents. (7.1)
- CYP2D6 Inhibitors are likely to increase metoprolol concentration. (7.2)
- Concomitant use of glycosides, clonidine, and diltiazem and verapamil with beta-blockers can increase the risk of bradycardia. (7.3)
- Beta-blockers including metoprolol, may exacerbate the rebound hypertension that can follow the withdrawal of clonidine. (7.3)

8 USE IN SPECIFIC POPULATIONS

- Pregnancy: There are no adequate and well-controlled studies in pregnant women. Use this drug during pregnancy only if clearly needed. (8.1)
- Nursing Mothers: Consider possible infant exposure. (8.3)
- Pediatrics: Safety and effectiveness have not been established in patients < 6 years of age. (8.4)
- Geriatrics: No notable difference in efficacy or safety vs. younger patients. (8.5)
- Hepatic Impairment: Consider initiating TOPROL-XL therapy at low doses and gradually increase dosage to optimize therapy, while monitoring closely for adverse events. (8.6)

FULL PRESCRIBING INFORMATION

WARNING: ISCHEMIC HEART DISEASE

Following abrupt cessation of therapy with certain beta-blocking agents, exacerbations of angina pectoris and, in some cases, myocardial infarction have occurred. When discontinuing chronically administered TOPROL-XL, particularly in patients with ischemic heart disease, the dosage should be gradually reduced over a period of 1 - 2 weeks and the patient should be carefully monitored. If angina markedly worsens or acute coronary insufficiency develops, TOPROL-XL administration should be reinstated promptly, at least temporarily, and other measures appropriate for the management of unstable angina should be taken. Warn patients against interruption or discontinuation of therapy without the physician’s advice. Because coronary artery disease is common and may be unrecognized, it may be prudent not to discontinue TOPROL-XL therapy abruptly even in patients treated only for hypertension (5.1).

1 INDICATIONS AND USAGE

1.1 Hypertension

TOPROL-XL is indicated for the treatment of hypertension, to lower blood pressure. Lowering blood pressure lowers the risk of fatal and non-fatal cardiovascular events, primarily strokes and myocardial infarctions. These benefits have been seen in controlled trials of antihypertensive drugs from a wide variety of pharmacologic classes including metoprolol.

Control of high blood pressure should be part of comprehensive cardiovascular risk management, including, as appropriate, lipid control, diabetes management, antithrombotic therapy, smoking cessation, exercise, and limited sodium intake. Many patients will require more than 1 drug to achieve blood pressure goals. For specific advice on goals and management, see published guidelines, such as those of the National High Blood Pressure Education Program’s Joint National Committee on Prevention, Detection, Evaluation, and Treatment of High Blood Pressure (JNC).

Numerous antihypertensive drugs, from a variety of pharmacologic classes and with different mechanisms of action, have been shown in randomized controlled trials to reduce cardiovascular morbidity and mortality, and it can be concluded that it is blood pressure reduction, and not some other pharmacologic property of the drugs, that is largely responsible for those benefits. The largest and most consistent cardiovascular outcome benefit has been a reduction in the risk of stroke, but reductions in myocardial infarction and cardiovascular mortality also have been seen regularly.

Elevated systolic or diastolic pressure causes increased cardiovascular risk, and the absolute risk increase per mmHg is greater at higher blood pressures, so that even modest reductions of severe hypertension can provide substantial benefit. Relative risk reduction from blood pressure reduction is similar across populations with varying absolute risk, so the absolute benefit is greater in patients who are at higher risk independent of their hypertension (for example, patients with diabetes or hyperlipidemia), and such patients would be expected to benefit from more aggressive treatment to a lower blood pressure goal.

Some antihypertensive drugs have smaller blood pressure effects (as monotherapy) in black patients, and many antihypertensive drugs have additional approved indications and effects (e.g., on angina, heart failure, or diabetic kidney disease). These considerations may guide selection of therapy.

TOPROL-XL may be administered with other antihypertensive agents.

1.2 Angina Pectoris

TOPROL-XL is indicated in the long-term treatment of angina pectoris, to reduce angina attacks and to improve exercise tolerance.

1.3 Heart Failure

TOPROL-XL is indicated for the treatment of stable, symptomatic (NYHA Class II or III) heart failure of ischemic, hypertensive, or cardiomyopathic origin. It was studied in patients already receiving ACE inhibitors, diuretics, and, in the majority of cases, digitalis. In this population, TOPROL-XL decreased the rate of mortality plus hospitalization, largely through a reduction in cardiovascular mortality and hospitalizations for heart failure.

2 DOSAGE AND ADMINISTRATION

TOPROL-XL is an extended-release tablet intended for once daily administration. For treatment of hypertension and angina, when switching from immediate-release metoprolol to TOPROL-XL, use the same total daily dose of TOPROL-XL. Individualize the dosage of TOPROL-XL. Titration may be needed in some patients.

TOPROL-XL tablets are scored and can be divided; however, do not crush or chew the whole or half tablet.

2.1 Hypertension

Adults: The usual initial dosage is 25 to 100 mg daily in a single dose. The dosage may be increased at weekly (or longer) intervals until optimum blood pressure reduction is achieved. In general, the maximum effect of any given dosage level will be apparent after 1 week of therapy. Dosages above 400 mg per day have not been studied.

Pediatric Hypertensive Patients ≥ 6 Years of age: A pediatric clinical hypertension study in patients 6 to 16 years of age did not meet its primary endpoint (dose response for reduction in SBP); however, some other endpoints demonstrated effectiveness [see Use in Specific Populations (8.4)]. If selected for treatment, the recommended starting dose of TOPROL-XL is 1 mg/kg once daily, but the maximum initial dose should not exceed 50 mg once daily. Dosage should be adjusted according to blood pressure response. Doses above 2 mg/kg (or in excess of 200 mg) once daily have not been studied in pediatric patients [see Clinical Pharmacology (12.3)].

TOPROL-XL is not recommended in pediatric patients < 6 years of age [see Use in Specific Populations (8.4)].

2.2 Angina Pectoris

Individualize the dosage of TOPROL-XL. The usual initial dosage is 100 mg daily, given in a single dose. Gradually increase the dosage at weekly intervals until optimum clinical response has been obtained or there is a pronounced slowing of the heart rate. Dosages above 400 mg per day have not been studied. If treatment is to be discontinued, reduce the dosage gradually over a period of 1 - 2 weeks [see Warnings and Precautions (5)].

2.3 Heart Failure

Dosage must be individualized and closely monitored during up-titration. Prior to initiation of TOPROL-XL, stabilize the dose of other heart failure drug therapy. The recommended starting dose of TOPROL-XL is 25 mg once daily for two weeks in patients with NYHA Class II heart failure and 12.5 mg once daily in patients with more severe heart failure. Double the dose every two weeks to the highest dosage level tolerated by the patient or up to 200 mg of TOPROL-XL. Initial difficulty with titration should not preclude later attempts to introduce TOPROL-XL. If patients experience symptomatic bradycardia, reduce the dose of TOPROL-XL. If transient worsening of heart failure occurs, consider treating with increased doses of diuretics, lowering the dose of TOPROL-XL or temporarily discontinuing it. The dose of TOPROL-XL should not be increased until symptoms of worsening heart failure have been stabilized.

3 DOSAGE FORMS AND STRENGTHS

25 mg tablets White, oval, biconvex, film-coated scored tablet engraved with “A/β”.

50 mg tablets: White, round, biconvex, film-coated scored tablet engraved with “A/mo”.

100 mg tablets: White, round, biconvex, film-coated scored tablet engraved with “A/ms”.

200 mg tablets: White, oval, biconvex, film-coated scored tablet engraved with “A/my”.

4 CONTRAINDICATIONS

TOPROL-XL is contraindicated in severe bradycardia, second or third degree heart block, cardiogenic shock, decompensated cardiac failure, sick sinus syndrome (unless a permanent pacemaker is in place), and in patients who are hypersensitive to any component of this product.

5 WARNINGS AND PRECAUTIONS

5.1 Ischemic Heart Disease

Following abrupt cessation of therapy with certain beta-blocking agents, exacerbations of angina pectoris and, in some cases, myocardial infarction have occurred. When discontinuing chronically administered TOPROL-XL, particularly in patients with ischemic heart disease, gradually reduce the dosage over a period of 1 - 2 weeks and monitor the patient. If angina markedly worsens or acute coronary ischemia develops, promptly reinstate TOPROL-XL, and take measures appropriate for the management of unstable angina. Warn patients not to interrupt therapy without their physician’s advice. Because coronary artery disease is common and may be unrecognized, avoid abruptly discontinuing TOPROL-XL in patients treated only for hypertension.

5.2 Heart Failure

Worsening cardiac failure may occur during up-titration of TOPROL-XL. If such symptoms occur, increase diuretics and restore clinical stability before advancing the dose of TOPROL-XL [see Dosage and Administration (2)]. It may be necessary to lower the dose of TOPROL-XL or temporarily discontinue it. Such episodes do not preclude subsequent successful titration of TOPROL-XL.

5.3 Bronchospastic Disease

PATIENTS WITH BRONCHOSPASTIC DISEASES SHOULD, IN GENERAL, NOT RECEIVE BETA-BLOCKERS. Because of its relative beta1 cardio-selectivity, however, TOPROL-XL may be used in patients with bronchospastic disease who do not respond to, or cannot tolerate, other antihypertensive treatment. Because beta1-selectivity is not absolute, use the lowest possible dose of TOPROL-XL. Bronchodilators, including beta2-agonists, should be readily available or administered concomitantly [see Dosage and Administration (2)].

5.4 Pheochromocytoma

If TOPROL-XL is used in the setting of pheochromocytoma, it should be given in combination with an alpha blocker, and only after the alpha blocker has been initiated. Administration of beta-blockers alone in the setting of pheochromocytoma has been associated with a paradoxical increase in blood pressure due to the attenuation of beta-mediated vasodilatation in skeletal muscle.

5.5 Major Surgery

Avoid initiation of a high-dose regimen of extended-release metoprolol in patients undergoing non-cardiac surgery, since such use in patients with cardiovascular risk factors has been associated with bradycardia, hypotension, stroke and death.

Chronically administered beta-blocking therapy should not be routinely withdrawn prior to major surgery, however, the impaired ability of the heart to respond to reflex adrenergic stimuli may augment the risks of general anesthesia and surgical procedures.

5.6 Diabetes and Hypoglycemia

Beta-blockers may mask tachycardia occurring with hypoglycemia, but other manifestations such as dizziness and sweating may not be significantly affected.

5.7 Hepatic Impairment

Consider initiating TOPROL-XL therapy at doses lower than those recommended for a given indication; gradually increase dosage to optimize therapy, while monitoring closely for adverse events.

5.8 Thyrotoxicosis

Beta-adrenergic blockade may mask certain clinical signs of hyperthyroidism, such as tachycardia. Abrupt withdrawal of beta-blockade may precipitate a thyroid storm.

5.9 Anaphylactic Reaction

While taking beta-blockers, patients with a history of severe anaphylactic reactions to a variety of allergens may be more reactive to repeated challenge and may be unresponsive to the usual doses of epinephrine used to treat an allergic reaction.

5.10 Peripheral Vascular Disease

Beta-blockers can precipitate or aggravate symptoms of arterial insufficiency in patients with peripheral vascular disease.

5.11 Calcium Channel Blockers

Because of significant inotropic and chronotropic effects in patients treated with beta-blockers and calcium channel blockers of the verapamil and diltiazem type, caution should be exercised in patients treated with these agents concomitantly.

6 ADVERSE REACTIONS

The following adverse reactions are described elsewhere in labeling:

- Worsening angina or myocardial infarction [see Warnings and Precautions (5)].
- Worsening heart failure [see Warnings and Precautions (5)].
- Worsening AV block [see Contraindications (4)].

6.1 Clinical Trials Experience

Because clinical trials are conducted under widely varying conditions, adverse reaction rates observed in the clinical trials of a drug cannot be directly compared to rates in the clinical trials of another drug and may not reflect the rates observed in practice. The adverse reaction information from clinical trials does, however, provide a basis for identifying the adverse events that appear to be related to drug use and for approximating rates.

Hypertension and Angina: Most adverse reactions have been mild and transient. The most common (>2%) adverse reactions are tiredness, dizziness, depression, diarrhea, shortness of breath, bradycardia, and rash.

Heart Failure: In the MERIT-HF study comparing TOPROL-XL in daily doses up to 200 mg (mean dose 159 mg once-daily; n=1990) to placebo (n=2001), 10.3% of TOPROL-XL patients discontinued for adverse reactions vs. 12.2% of placebo patients.

The table below lists adverse reactions in the MERIT-HF study that occurred at an incidence of ≥ 1% in the TOPROL-XL group and greater than placebo by more than 0.5%, regardless of the assessment of causality.

Adverse Reactions Occurring in the MERIT-HF Study at an Incidence ≥1% in the TOPROL-XL Group and Greater Than Placebo by More Than 0.5%
 | TOPROL-XL; n=1990 % of patients | Placebo; n=2001 % of patients
Dizziness/vertigo | 1.8 | 1.0
Bradycardia | 1.5 | 0.4
Accident and/or injury | 1.4 | 0.8

Post-operative Adverse Events: In a randomized, double-blind, placebo-controlled trial of 8351 patients with or at risk for atherosclerotic disease undergoing non-vascular surgery and who were not taking beta–blocker therapy, TOPROL-XL 100 mg was started 2 to 4 hours prior to surgery then continued for 30 days at 200 mg per day. TOPROL-XL use was associated with a higher incidence of bradycardia (6.6% vs. 2.4%; HR, 2.74; 95% CI 2.19, 3.43), hypotension (15% vs. 9.7%; HR 1.55; 95% CI 1.37, 1.74), stroke (1.0% vs. 0.5%; HR 2.17; 95% CI 1.26, 3.74) and death (3.1% vs. 2.3%; HR 1.33; 95% CI 1.03, 1.74) compared to placebo.

6.2 Post-Marketing Experience

The following adverse reactions have been identified during post-approval use of TOPROL-XL or immediate-release metoprolol. Because these reactions are reported voluntarily from a population of uncertain size, it is not always possible to reliably estimate their frequency or establish a causal relationship to drug exposure.

Cardiovascular: Cold extremities, arterial insufficiency (usually of the Raynaud type), palpitations, peripheral edema, syncope, chest pain and hypotension.

Respiratory: Wheezing (bronchospasm), dyspnea.

Central Nervous System: Confusion, short-term memory loss, headache, somnolence, nightmares, insomnia, anxiety/nervousness, hallucinations, paresthesia.

Gastrointestinal: Nausea, dry mouth, constipation, flatulence, heartburn, hepatitis, vomiting.

Hypersensitive Reactions: Pruritus.

Miscellaneous: Musculoskeletal pain, arthralgia, blurred vision, decreased libido, male impotence, tinnitus, reversible alopecia, agranulocytosis, dry eyes, worsening of psoriasis, Peyronie’s disease, sweating, photosensitivity, taste disturbance.

Potential Adverse Reactions: In addition, there are adverse reactions not listed above that have been reported with other beta-adrenergic blocking agents and should be considered potential adverse reactions to TOPROL-XL.

Central Nervous System: Reversible mental depression progressing to catatonia; an acute reversible syndrome characterized by disorientation for time and place, short-term memory loss, emotional lability, clouded sensorium, and decreased performance on neuropsychometrics.

Hematologic: Agranulocytosis, nonthrombocytopenic purpura, thrombocytopenic purpura.

Hypersensitive Reactions: Laryngospasm, respiratory distress.

6.3 Laboratory Test Findings

Clinical laboratory findings may include elevated levels of serum transaminase, alkaline phosphatase, and lactate dehydrogenase.

7 DRUG INTERACTIONS

7.1 Catecholamine Depleting Drugs

Catecholamine depleting drugs (e.g., reserpine, monoamine oxidase (MAO) inhibitors) may have an additive effect when given with beta-blocking agents. Observe patients treated with TOPROL-XL plus a catecholamine depletor for evidence of hypotension or marked bradycardia, which may produce vertigo, syncope, or postural hypotension.

7.2 CYP2D6 Inhibitors

Drugs that inhibit CYP2D6 such as quinidine, fluoxetine, paroxetine, and propafenone are likely to increase metoprolol concentration. In healthy subjects with CYP2D6 extensive metabolizer phenotype, coadministration of quinidine 100 mg and immediate-release metoprolol 200 mg tripled the concentration of S-metoprolol and doubled the metoprolol elimination half-life. In four patients with cardiovascular disease, coadministration of propafenone 150 mg t.i.d. with immediate-release metoprolol 50 mg t.i.d. resulted in two- to five-fold increases in the steady-state concentration of metoprolol. These increases in plasma concentration would decrease the cardioselectivity of metoprolol.

7.3 Digitalis, Clonidine, and Calcium Channel Blockers

Digitalis glycosides, clonidine, diltiazem and verapamil slow atrioventricular conduction and decrease heart rate. Concomitant use with beta blockers can increase the risk of bradycardia.

If clonidine and a beta blocker, such as metoprolol are coadministered, withdraw the beta-blocker several days before the gradual withdrawal of clonidine because beta-blockers may exacerbate the rebound hypertension that can follow the withdrawal of clonidine. If replacing clonidine by beta-blocker therapy, delay the introduction of beta-blockers for several days after clonidine administration has stopped [see Warnings and Precautions (5.11)].

8 USE IN SPECIFIC POPULATIONS

8.1 Pregnancy

Pregnancy Category C

Metoprolol tartrate has been shown to increase post-implantation loss and decrease neonatal survival in rats at doses up to 22 times, on a mg/m^2 basis, the daily dose of 200 mg in a 60-kg patient. Distribution studies in mice confirm exposure of the fetus when metoprolol tartrate is administered to the pregnant animal. These studies have revealed no evidence of impaired fertility or teratogenicity. There are no adequate and well-controlled studies in pregnant women. Because animal reproduction studies are not always predictive of human response, use this drug during pregnancy only if clearly needed.

8.3 Nursing Mothers

Metoprolol is excreted in breast milk in very small quantities. An infant consuming 1 liter of breast milk daily would receive a dose of less than 1 mg of the drug. Consider possible infant exposure when TOPROL-XL is administered to a nursing woman.

8.4 Pediatric Use

One hundred forty-four hypertensive pediatric patients aged 6 to 16 years were randomized to placebo or to one of three dose levels of TOPROL-XL (0.2, 1.0 or 2.0 mg/kg once daily) and followed for 4 weeks. The study did not meet its primary endpoint (dose response for reduction in SBP). Some pre-specified secondary endpoints demonstrated effectiveness including:

- Dose-response for reduction in DBP,
- 1 mg/kg vs. placebo for change in SBP, and
- 2 mg/kg vs. placebo for change in SBP and DBP.

The mean placebo corrected reductions in SBP ranged from 3 to 6 mmHg, and DBP from 1 to 5 mmHg. Mean reduction in heart rate ranged from 5 to 7 bpm but considerably greater reductions were seen in some individuals [see Dosage and Administration (2.1)].

No clinically relevant differences in the adverse event profile were observed for pediatric patients aged 6 to 16 years as compared with adult patients.

Safety and effectiveness of TOPROL-XL have not been established in patients < 6 years of age.

8.5 Geriatric Use

Clinical studies of TOPROL-XL in hypertension did not include sufficient numbers of subjects aged 65 and over to determine whether they respond differently from younger subjects. Other reported clinical experience in hypertensive patients has not identified differences in responses between elderly and younger patients.

Of the 1,990 patients with heart failure randomized to TOPROL-XL in the MERIT-HF trial, 50% (990) were 65 years of age and older and 12% (238) were 75 years of age and older. There were no notable differences in efficacy or the rate of adverse reactions between older and younger patients.

In general, use a low initial starting dose in elderly patients given their greater frequency of decreased hepatic, renal, or cardiac function, and of concomitant disease or other drug therapy.

8.6 Hepatic Impairment

No studies have been performed with TOPROL-XL in patients with hepatic impairment. Because TOPROL-XL is metabolized by the liver, metoprolol blood levels are likely to increase substantially with poor hepatic function. Therefore, initiate therapy at doses lower than those recommended for a given indication; and increase doses gradually in patients with impaired hepatic function.

8.7 Renal Impairment

The systemic availability and half-life of metoprolol in patients with renal failure do not differ to a clinically significant degree from those in normal subjects. No reduction in dosage is needed in patients with chronic renal failure [see Clinical Pharmacology (12.3)].

10 OVERDOSAGE

Signs and Symptoms - Overdosage of TOPROL-XL may lead to severe bradycardia, hypotension, and cardiogenic shock. Clinical presentation can also include: atrioventricular block, heart failure, bronchospasm, hypoxia, impairment of consciousness/coma, nausea and vomiting.

Treatment – Consider treating the patient with intensive care. Patients with myocardial infarction or heart failure may be prone to significant hemodynamic instability. Seek consultation with a regional poison control center and a medical toxicologist as needed. Beta-blocker overdose may result in significant resistance to resuscitation with adrenergic agents, including beta-agonists. On the basis of the pharmacologic actions of metoprolol, employ the following measures.

There is very limited experience with the use of hemodialysis to remove metoprolol, however metoprolol is not highly protein bound.

Bradycardia: Evaluate the need for atropine, adrenergic-stimulating drugs or pacemaker to treat bradycardia and conduction disorders.

Hypotension: Treat underlying bradycardia. Consider intravenous vasopressor infusion, such as dopamine or norepinephrine.

Heart failure and shock: May be treated when appropriate with suitable volume expansion, injection of glucagon (if necessary, followed by an intravenous infusion of glucagon), intravenous administration of adrenergic drugs such as dobutamine, with α1 receptor agonistic drugs added in presence of vasodilation.

Bronchospasm: Can usually be reversed by bronchodilators.

11 DESCRIPTION

TOPROL-XL, metoprolol succinate, is a beta1-selective (cardioselective) adrenoceptor blocking agent, for oral administration, available as extended-release tablets. TOPROL-XL has been formulated to provide a controlled and predictable release of metoprolol for once-daily administration. The tablets comprise a multiple unit system containing metoprolol succinate in a multitude of controlled release pellets. Each pellet acts as a separate drug delivery unit and is designed to deliver metoprolol continuously over the dosage interval. The tablets contain 23.75, 47.5, 95 and 190 mg of metoprolol succinate equivalent to 25, 50, 100 and 200 mg of metoprolol tartrate, USP, respectively. Its chemical name is (±)1- (isopropylamino)-3-[p-(2-methoxyethyl) phenoxy]-2-propanol succinate (2:1) (salt). Its structural formula is:

Metoprolol succinate is a white crystalline powder with a molecular weight of 652.8. It is freely soluble in water; soluble in methanol; sparingly soluble in ethanol; slightly soluble in dichloromethane and 2-propanol; practically insoluble in ethyl-acetate, acetone, diethylether and heptane. Inactive ingredients: silicon dioxide, cellulose compounds, sodium stearyl fumarate, polyethylene glycol, titanium dioxide, paraffin.

12 CLINICAL PHARMACOLOGY

12.1 Mechanism of Action

Hypertension: The mechanism of the antihypertensive effects of beta-blocking agents has not been elucidated. However, several possible mechanisms have been proposed: (1) competitive antagonism of catecholamines at peripheral (especially cardiac) adrenergic neuron sites, leading to decreased cardiac output; (2) a central effect leading to reduced sympathetic outflow to the periphery; and (3) suppression of renin activity.

Heart Failure: The precise mechanism for the beneficial effects of beta-blockers in heart failure has not been elucidated.

12.2 Pharmacodynamics

Clinical pharmacology studies have confirmed the beta-blocking activity of metoprolol in man, as shown by (1) reduction in heart rate and cardiac output at rest and upon exercise, (2) reduction of systolic blood pressure upon exercise, (3) inhibition of isoproterenol-induced tachycardia, and (4) reduction of reflex orthostatic tachycardia.

Metoprolol is a beta1-selective (cardioselective) adrenergic receptor blocking agent. This preferential effect is not absolute, however, and at higher plasma concentrations, metoprolol also inhibits beta2-adrenoreceptors, chiefly located in the bronchial and vascular musculature. Metoprolol has no intrinsic sympathomimetic activity, and membrane-stabilizing activity is detectable only at plasma concentrations much greater than required for beta-blockade. Animal and human experiments indicate that metoprolol slows the sinus rate and decreases AV nodal conduction.

The relative beta1-selectivity of metoprolol has been confirmed by the following: (1) In normal subjects, metoprolol is unable to reverse the beta2-mediated vasodilating effects of epinephrine. This contrasts with the effect of nonselective beta-blockers, which completely reverse the vasodilating effects of epinephrine. (2) In asthmatic patients, metoprolol reduces FEV1 and FVC significantly less than a nonselective beta-blocker, propranolol, at equivalent beta1-receptor blocking doses.

The relationship between plasma metoprolol levels and reduction in exercise heart rate is independent of the pharmaceutical formulation. Using an Emax model, the maximum effect is a 30% reduction in exercise heart rate, which is attributed to beta1-blockade. Beta1-blocking effects in the range of 30-80% of the maximal effect (approximately 8-23% reduction in exercise heart rate) correspond to metoprolol plasma concentrations from 30-540 nmol/L. The relative beta1-selectivity of metoprolol diminishes and blockade of beta2-adrenoceptors increases at plasma concentration above 300 nmol/L.

Although beta-adrenergic receptor blockade is useful in the treatment of angina, hypertension, and heart failure there are situations in which sympathetic stimulation is vital. In patients with severely damaged hearts, adequate ventricular function may depend on sympathetic drive. In the presence of AV block, beta-blockade may prevent the necessary facilitating effect of sympathetic activity on conduction. Beta2-adrenergic blockade results in passive bronchial constriction by interfering with endogenous adrenergic bronchodilator activity in patients subject to bronchospasm and may also interfere with exogenous bronchodilators in such patients.

In other studies, treatment with TOPROL-XL produced an improvement in left ventricular ejection fraction. TOPROL-XL was also shown to delay the increase in left ventricular end-systolic and end-diastolic volumes after 6 months of treatment.

12.3 Pharmacokinetics

Adults: In man, absorption of metoprolol is rapid and complete. Plasma levels following oral administration of conventional metoprolol tablets, however, approximate 50% of levels following intravenous administration, indicating about 50% first-pass metabolism. Metoprolol crosses the blood-brain barrier and has been reported in the CSF in a concentration 78% of the simultaneous plasma concentration.

Plasma levels achieved are highly variable after oral administration. Only a small fraction of the drug (about 12%) is bound to human serum albumin. Metoprolol is a racemic mixture of R- and S- enantiomers, and is primarily metabolized by CYP2D6. When administered orally, it exhibits stereoselective metabolism that is dependent on oxidation phenotype. Elimination is mainly by biotransformation in the liver, and the plasma half-life ranges from approximately 3 to 7 hours. Less than 5% of an oral dose of metoprolol is recovered unchanged in the urine; the rest is excreted by the kidneys as metabolites that appear to have no beta-blocking activity.

Following intravenous administration of metoprolol, the urinary recovery of unchanged drug is approximately 10%. The systemic availability and half-life of metoprolol in patients with renal failure do not differ to a clinically significant degree from those in normal subjects. Consequently, no reduction in metoprolol succinate dosage is usually needed in patients with chronic renal failure.

Metoprolol is metabolized predominantly by CYP2D6, an enzyme that is absent in about 8% of Caucasians (poor metabolizers) and about 2% of most other populations. CYP2D6 can be inhibited by a number of drugs. Poor metabolizers and extensive metabolizers who concomitantly use CYP2D6 inhibiting drugs will have increased (several-fold) metoprolol blood levels, decreasing metoprolol's cardioselectivity [see Drug Interactions (7.2)].

In comparison to conventional metoprolol, the plasma metoprolol levels following administration of TOPROL-XL are characterized by lower peaks, longer time to peak and significantly lower peak to trough variation. The peak plasma levels following once-daily administration of TOPROL-XL average one-fourth to one-half the peak plasma levels obtained following a corresponding dose of conventional metoprolol, administered once daily or in divided doses. At steady state the average bioavailability of metoprolol following administration of TOPROL-XL, across the dosage range of 50 to 400 mg once daily, was 77% relative to the corresponding single or divided doses of conventional metoprolol. Nevertheless, over the 24-hour dosing interval, β1-blockade is comparable and dose-related [see Clinical Pharmacology (12)]. The bioavailability of metoprolol shows a dose-related, although not directly proportional, increase with dose and is not significantly affected by food following TOPROL-XL administration.

Pediatrics: The pharmacokinetic profile of TOPROL-XL was studied in 120 pediatric hypertensive patients (6-17 years of age) receiving doses ranging from 12.5 to 200 mg once daily. The pharmacokinetics of metoprolol were similar to those described previously in adults. Age, gender, race, and ideal body weight had no significant effects on metoprolol pharmacokinetics. Metoprolol apparent oral clearance (CL/F) increased linearly with body weight. Metoprolol pharmacokinetics have not been investigated in patients < 6 years of age.

13 NONCLINICAL TOXICOLOGY

13.1 Carcinogenesis, Mutagenesis, Impairment of Fertility

Long-term studies in animals have been conducted to evaluate the carcinogenic potential of metoprolol tartrate. In 2-year studies in rats at three oral dosage levels of up to 800 mg/kg/day (41 times, on a mg/m^2 basis, the daily dose of 200 mg for a 60-kg patient), there was no increase in the development of spontaneously occurring benign or malignant neoplasms of any type. The only histologic changes that appeared to be drug related were an increased incidence of generally mild focal accumulation of foamy macrophages in pulmonary alveoli and a slight increase in biliary hyperplasia. In a 21-month study in Swiss albino mice at three oral dosage levels of up to 750 mg/kg/day (18 times, on a mg/m^2 basis, the daily dose of 200 mg for a 60-kg patient), benign lung tumors (small adenomas) occurred more frequently in female mice receiving the highest dose than in untreated control animals. There was no increase in malignant or total (benign plus malignant) lung tumors, nor in the overall incidence of tumors or malignant tumors. This 21-month study was repeated in CD-1 mice, and no statistically or biologically significant differences were observed between treated and control mice of either sex for any type of tumor.

All genotoxicity tests performed on metoprolol tartrate (a dominant lethal study in mice, chromosome studies in somatic cells, a Salmonella/mammalian-microsome mutagenicity test, and a nucleus anomaly test in somatic interphase nuclei) and metoprolol succinate (a Salmonella/mammalian-microsome mutagenicity test) were negative.

No evidence of impaired fertility due to metoprolol tartrate was observed in a study performed in rats at doses up to 22 times, on a mg/m^2 basis, the daily dose of 200 mg in a 60-kg patient.

14 CLINICAL STUDIES

In five controlled studies in normal healthy subjects, the same daily doses of TOPROL-XL and immediate-release metoprolol were compared in terms of the extent and duration of beta1- blockade produced. Both formulations were given in a dose range equivalent to 100-400 mg of immediate-release metoprolol per day. In these studies, TOPROL-XL was administered once a day and immediate-release metoprolol was administered once to four times a day. A sixth controlled study compared the beta1-blocking effects of a 50 mg daily dose of the two formulations. In each study, beta1-blockade was expressed as the percent change from baseline in exercise heart rate following standardized submaximal exercise tolerance tests at steady state. TOPROL-XL administered once a day, and immediate-release metoprolol administered once to four times a day, provided comparable total beta1-blockade over 24 hours (area under the beta1-blockade versus time curve) in the dose range 100-400 mg. At a dosage of 50 mg once daily, TOPROL-XL produced significantly higher total beta1-blockade over 24 hours than immediate-release metoprolol. For TOPROL-XL, the percent reduction in exercise heart rate was relatively stable throughout the entire dosage interval and the level of beta1-blockade increased with increasing doses from 50 to 300 mg daily. The effects at peak/trough (i.e., at 24-hours post-dosing) were: 14/9, 16/10, 24/14, 27/22 and 27/20% reduction in exercise heart rate for doses of 50, 100, 200, 300 and 400 mg TOPROL-XL once a day, respectively. In contrast to TOPROL-XL, immediate-release metoprolol given at a dose of 50-100 mg once a day produced a significantly larger peak effect on exercise tachycardia, but the effect was not evident at 24 hours. To match the peak to trough ratio obtained with TOPROL-XL over the dosing range of 200 to 400 mg, a t.i.d. to q.i.d. divided dosing regimen was required for immediate-release metoprolol. A controlled cross-over study in heart failure patients compared the plasma concentrations and beta1-blocking effects of 50 mg immediate-release metoprolol administered t.i.d., 100 mg and 200 mg TOPROL-XL once daily. A 50 mg dose of immediate-release metoprolol t.i.d. produced a peak plasma level of metoprolol similar to the peak level observed with 200 mg of TOPROL-XL. A 200 mg dose of TOPROL-XL produced a larger effect on suppression of exercise-induced and Holter-monitored heart rate over 24 hours compared to 50 mg t.i.d. of immediate-release metoprolol.

In a double-blind study, 1092 patients with mild-to-moderate hypertension were randomized to once daily TOPROL-XL (25, 100, or 400 mg), PLENDIL® (felodipine extended-release tablets), the combination, or placebo. After 9 weeks, TOPROL-XL alone decreased sitting blood pressure by 6-8/4-7 mmHg (placebo-corrected change from baseline) at 24 hours post-dose. The combination of TOPROL-XL with PLENDIL has greater effects on blood pressure.

In controlled clinical studies, an immediate-release dosage form of metoprolol was an effective antihypertensive agent when used alone or as concomitant therapy with thiazide-type diuretics at dosages of 100-450 mg daily. TOPROL-XL, in dosages of 100 to 400 mg once daily, produces similar β1-blockade as conventional metoprolol tablets administered two to four times daily. In addition, TOPROL-XL administered at a dose of 50 mg once daily lowered blood pressure 24-hours post-dosing in placebo-controlled studies. In controlled, comparative, clinical studies, immediate-release metoprolol appeared comparable as an antihypertensive agent to propranolol, methyldopa, and thiazide-type diuretics, and affected both supine and standing blood pressure. Because of variable plasma levels attained with a given dose and lack of a consistent relationship of antihypertensive activity to drug plasma concentration, selection of proper dosage requires individual titration.

14.1 Angina Pectoris

By blocking catecholamine-induced increases in heart rate, in velocity and extent of myocardial contraction, and in blood pressure, metoprolol reduces the oxygen requirements of the heart at any given level of effort, thus making it useful in the long-term management of angina pectoris.

In controlled clinical trials, an immediate-release formulation of metoprolol has been shown to be an effective antianginal agent, reducing the number of angina attacks and increasing exercise tolerance. The dosage used in these studies ranged from 100 to 400 mg daily. TOPROL-XL, in dosages of 100 to 400 mg once daily, has been shown to possess beta-blockade similar to conventional metoprolol tablets administered two to four times daily.

14.2 Heart Failure

MERIT-HF was a double-blind, placebo-controlled study of TOPROL-XL conducted in 14 countries including the US. It randomized 3991 patients (1990 to TOPROL-XL) with ejection fraction ≤0.40 and NYHA Class II-IV heart failure attributable to ischemia, hypertension, or cardiomyopathy. The protocol excluded patients with contraindications to beta-blocker use, those expected to undergo heart surgery, and those within 28 days of myocardial infarction or unstable angina. The primary endpoints of the trial were (1) all-cause mortality plus all-cause hospitalization (time to first event) and (2) all-cause mortality. Patients were stabilized on optimal concomitant therapy for heart failure, including diuretics, ACE inhibitors, cardiac glycosides, and nitrates. At randomization, 41% of patients were NYHA Class II; 55% NYHA Class III; 65% of patients had heart failure attributed to ischemic heart disease; 44% had a history of hypertension; 25% had diabetes mellitus; 48% had a history of myocardial infarction. Among patients in the trial, 90% were on diuretics, 89% were on ACE inhibitors, 64% were on digitalis, 27% were on a lipid-lowering agent, 37% were on an oral anticoagulant, and the mean ejection fraction was 0.28. The mean duration of follow-up was one year. At the end of the study, the mean daily dose of TOPROL-XL was 159 mg.

The trial was terminated early for a statistically significant reduction in all-cause mortality (34%, nominal p= 0.00009). The risk of all-cause mortality plus all-cause hospitalization was reduced by 19% (p= 0.00012). The trial also showed improvements in heart failure-related mortality and heart failure-related hospitalizations, and NYHA functional class.

The table below shows the principal results for the overall study population. The figure below illustrates principal results for a wide variety of subgroup comparisons, including US vs. non-US populations (the latter of which was not pre-specified). The combined endpoints of all-cause mortality plus all-cause hospitalization and of mortality plus heart failure hospitalization showed consistent effects in the overall study population and the subgroups, including women and the US population. However, in the US subgroup (n=1071) and women (n=898), overall mortality and cardiovascular mortality appeared less affected. Analyses of female and US patients were carried out because they each represented about 25% of the overall population. Nonetheless, subgroup analyses can be difficult to interpret and it is not known whether these represent true differences or chance effects.

Clinical Endpoints in the MERIT-HF Study
Clinical Endpoint | Number of Patients |  | Relative Risk (95% Cl) | Risk Reduction With TOPROL-XL | Nominal P-value
 | Placebo; n=2001 | TOPROL-XL; n=1990
All-cause mortality plus all-caused hospitalization [Time to first event] | 767 | 641 | 0.81(0.73- 0.90) | 19% | 0.00012
All-cause mortality | 217 | 145 | 0.66(0.53- 0.81) | 34% | 0.00009
All-cause mortality plus heart failure hospitalization | 439 | 311 | 0.69(0.60- 0.80) | 31% | 0.0000008
Cardiovascular mortality | 203 | 128 | 0.62(0.50- 0.78) | 38% | 0.000022
Sudden death | 132 | 79 | 0.59(0.45- 0.78) | 41% | 0.0002
Death due to worsening heart failure | 58 | 30 | 0.51(0.33- 0.79) | 49% | 0.0023
Hospitalizations due to worsening heart failure [Comparison of treatment groups examines the number of hospitalizations (Wilcoxon test); relative risk and risk reduction are not applicable.] | 451 | 317 | N/A | N/A | 0.0000076
Cardiovascular hospitalization | 773 | 649 | N/A | N/A | 0.00028

15 REFERENCES

1. Devereaux PJ, Yang H, Yusuf S, Guyatt G, Leslie K, Villar JC et al. Effects of extended-release metoprolol succinate in patients undergoing non-cardiac surgery (POISE trial): a randomised controlled trial. Lancet. 2008; 371:1839-47.

16 HOW SUPPLIED/STORAGE AND HANDLING

Tablets containing metoprolol succinate equivalent to the indicated weight of metoprolol tartrate, USP, are white, biconvex, film-coated, and scored.

Tablet | Shape | Engraving | Bottle of 30; NDC 70347- | Bottle of 100; NDC 70347- | Bottle of 1000; NDC 70347-
25 mg | Oval | A/; β | 025-01 | 025-02 | 025-03
50 mg | Round | A/; mo | 050-01 | 050-02 | 050-03
100 mg | Round | A/; ms | 100-01 | 100-02 | 100-03
200 mg | Oval | A/; my | 200-01 | 200-02 | 200-03

Store at 25°C (77°F). Excursions permitted to 15-30°C (59-86°F). (See USP Controlled Room Temperature.)

17 PATIENT COUNSELING INFORMATION

Advise patients to take TOPROL-XL regularly and continuously, as directed, preferably with or immediately following meals. If a dose is missed, the patient should take only the next scheduled dose (without doubling it). Patients should not interrupt or discontinue TOPROL-XL without consulting the physician.

Advise patients (1) to avoid operating automobiles and machinery or engaging in other tasks requiring alertness until the patient’s response to therapy with TOPROL-XL has been determined; (2) to contact the physician if any difficulty in breathing occurs; (3) to inform the physician or dentist before any type of surgery that he or she is taking TOPROL-XL.

Heart failure patients should be advised to consult their physician if they experience signs or symptoms of worsening heart failure such as weight gain or increasing shortness of breath.

TOPROL-XL and PLENDIL are trademarks of the AstraZeneca group of companies.

Manufactured for:
Aralez Pharmaceuticals US Inc.
300 Interpace Parkway, Building C3
Parsippany NJ 07054

© Aralez Pharmaceuticals US Inc. 2016

Repackaging Information

Please reference the How Supplied section listed above for a description of individual tablets. This drug product has been received by Aphena Pharma - TN in a manufacturer or distributor packaged configuration and repackaged in full compliance with all applicable cGMP regulations. The package configurations available from Aphena are listed below:

Count | 200 mg
45 | 71610-373-45
90 | 71610-373-60

Store between 20°-25°C (68°-77°F). See USP Controlled Room Temperature. Dispense in a tight light-resistant container as defined by USP. Keep this and all drugs out of the reach of children.

Repackaged by:
Cookeville, TN 38506
20200113JMH

PRINCIPAL DISPLAY PANEL - 200 mg

NDC 71610-373 - Metoprolol Succinate (TOPROL-XL) 200 mg Tablets - Rx Only